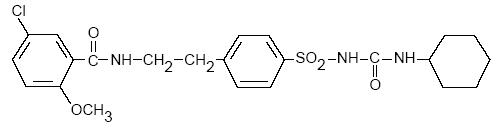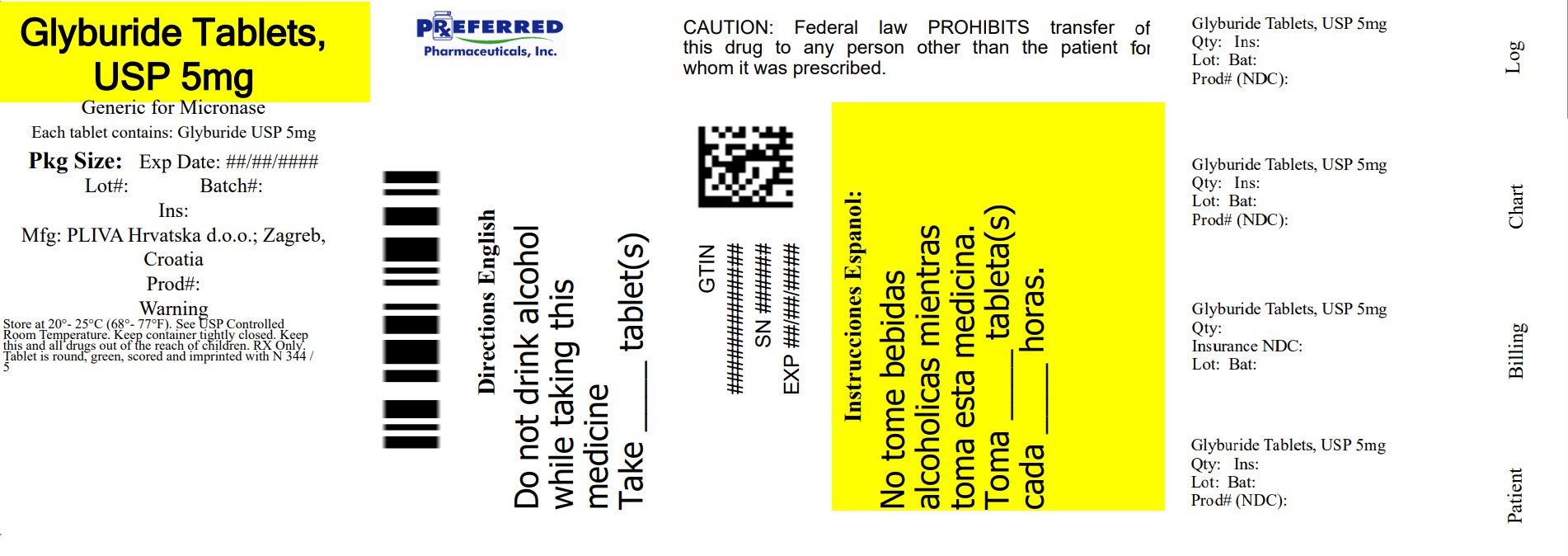 DRUG LABEL: Glyburide
NDC: 68788-4073 | Form: TABLET
Manufacturer: Preferred Pharmaceuticals Inc.
Category: prescription | Type: HUMAN PRESCRIPTION DRUG LABEL
Date: 20260127

ACTIVE INGREDIENTS: GLYBURIDE 5 mg/1 1
INACTIVE INGREDIENTS: MICROCRYSTALLINE CELLULOSE; STARCH, CORN; SODIUM STARCH GLYCOLATE TYPE A POTATO; SILICON DIOXIDE; MAGNESIUM STEARATE; D&C YELLOW NO. 10 ALUMINUM LAKE; FD&C BLUE NO. 1 ALUMINUM LAKE

GLYBURIDE TABLETS USP
1.25, 2.5, and 5 mg
8342
8343
8344
Rx only

DESCRIPTION

Glyburide tablets USP contain glyburide, USP, which is an oral blood-glucose-lowering drug of the sulfonylurea class. Glyburide, USP is a white, crystalline compound. The chemical name for glyburide, USP is 1-[[p-[2-(5-chloro-o-anisamido)ethyl]phenyl]-sulfonyl]-3-cyclohexylurea. It has the following structural formula:

C23H28ClN3O5S M.W. 493.99

Each tablet, for oral administration, contains 1.25 mg, 2.5 mg or 5 mg of glyburide, USP. In addition, each tablet contains the following inactive ingredients: microcrystalline cellulose, pregelatinized corn starch, sodium starch glycolate, colloidal silicon dioxide, and magnesium stearate. In addition, the 2.5 mg contains FD&C yellow No. 6 aluminum lake and the 5 mg contains D&C yellow No. 10 aluminum lake, and FD&C blue No. 1 aluminum lake.

CLINICAL PHARMACOLOGY

Actions

Glyburide appears to lower the blood glucose acutely by stimulating the release of insulin from the pancreas, an effect dependent upon functioning beta cells in the pancreatic islets. The mechanism by which glyburide lowers blood glucose during long-term administration has not been clearly established. With chronic administration in Type II diabetic patients, the blood glucose lowering effect persists despite a gradual decline in the insulin secretory response to the drug. Extrapancreatic effects may be involved in the mechanism of action of oral sulfonylurea hypoglycemic drugs. The combination of glyburide and metformin may have a synergistic effect, since both agents act to improve glucose tolerance by different but complementary mechanisms.

Some patients who are initially responsive to oral hypoglycemic drugs, including glyburide, may become unresponsive or poorly responsive over time. Alternatively, glyburide tablets may be effective in some patients who have become unresponsive to one or more other sulfonylurea drugs.

In addition to its blood glucose lowering actions, glyburide produces a mild diuresis by enhancement of renal free water clearance. Disulfiram-like reactions have very rarely been reported in patients treated with glyburide tablets.

Pharmacokinetics

Single dose studies with glyburide tablets in normal subjects demonstrate significant absorption of glyburide within one hour, peak drug levels at about four hours, and low but detectable levels at twenty-four hours. Mean serum levels of glyburide, as reflected by areas under the serum concentration-time curve, increase in proportion to corresponding increases in dose. Multiple dose studies with glyburide in diabetic patients demonstrate drug level concentration-time curves similar to single dose studies, indicating no buildup of drug in tissue depots. The decrease of glyburide in the serum of normal healthy individuals is biphasic; the terminal half-life is about 10 hours. In single dose studies in fasting normal subjects, the degree and duration of blood glucose lowering is proportional to the dose administered and to the area under the drug level concentration-time curve. The blood glucose lowering effect persists for 24 hours following single morning doses in nonfasting diabetic patients. Under conditions of repeated administration in diabetic patients, however, there is no reliable correlation between blood drug levels and fasting blood glucose levels. A one year study of diabetic patients treated with glyburide showed no reliable correlation between administered dose and serum drug level.

The major metabolite of glyburide is the 4-trans-hydroxy derivative. A second metabolite, the 3-cis-hydroxy derivative, also occurs. These metabolites probably contribute no significant hypoglycemic action in humans since they are only weakly active (1/400th and 1/40th as active, respectively, as glyburide) in rabbits.

Glyburide is excreted as metabolites in the bile and urine, approximately 50% by each route. This dual excretory pathway is qualitatively different from that of other sulfonylureas, which are excreted primarily in the urine.

Sulfonylurea drugs are extensively bound to serum proteins. Displacement from protein binding sites by other drugs may lead to enhanced hypoglycemic action. In vitro, the protein binding exhibited by glyburide is predominantly non-ionic, whereas that of other sulfonylureas (chlorpropamide, tolbutamide, tolazamide) is predominantly ionic. Acidic drugs such as phenylbutazone, warfarin, and salicylates displace the ionic-binding sulfonylureas from serum proteins to a far greater extent than the non-ionic binding glyburide. It has not been shown that this difference in protein binding will result in fewer drug-drug interactions with glyburide tablets in clinical use.

INDICATIONS AND USAGE

Glyburide tablets USP are indicated as an adjunct to diet and exercise to improve glycemic control in adults with type 2 diabetes mellitus.

CONTRAINDICATIONS

Glyburide tablets are contraindicated in patients with:

1. Known hypersensitivity or allergy to the drug.
2. Diabetic ketoacidosis, with or without coma. This condition should be treated with insulin.
3. Type I diabetes mellitus.
4. Concomitant administration of bosentan.

SPECIAL WARNING ON INCREASED RISK OF CARDIOVASCULAR MORTALITY

The administration of oral hypoglycemic drugs has been reported to be associated with increased cardiovascular mortality as compared to treatment with diet alone or diet plus insulin. This warning is based on the study conducted by the University Group Diabetes Program (UGDP), a long-term prospective clinical trial designed to evaluate the effectiveness of glucose-lowering drugs in preventing or delaying vascular complications in patients with non-insulin-dependent diabetes. The study involved 823 patients who were randomly assigned to one of four treatment groups.

UGDP reported that patients treated for 5 to 8 years with diet plus a fixed dose of tolbutamide (1.5 grams per day) had a rate of cardiovascular mortality approximately 2½ times that of patients treated with diet alone. A significant increase in total mortality was not observed, but the use of tolbutamide was discontinued based on the increase in cardiovascular mortality, thus limiting the opportunity for the study to show an increase in overall mortality. Despite controversy regarding the interpretation of these results, the findings of the UGDP study provide an adequate basis for this warning. The patient should be informed of the potential risks and advantages of glyburide and of alternative modes of therapy.

Although only one drug in the sulfonylurea class (tolbutamide) was included in this study, it is prudent from a safety standpoint to consider that this warning may also apply to other oral hypoglycemic drugs in this class, in view of their close similarities in mode of action and chemical structure.

PRECAUTIONS

Bioavailability studies have demonstrated that micronized glyburide tablets 3 mg provide serum glyburide concentrations that are not bioequivalent to those from nonmicronized glyburide tablets 5 mg. Therefore, patients should be retitrated when transferred from micronized glyburide tablets or other oral hypoglycemic agents.

General

Macrovascular Outcomes

There have been no clinical studies establishing conclusive evidence of macrovascular risk reduction with glyburide or any other anti-diabetic drug.

Hypoglycemia

All sulfonylureas including glyburide are capable of producing severe hypoglycemia. Proper patient selection and dosage and instructions are important to avoid hypoglycemic episodes. Renal or hepatic insufficiency may cause elevated drug levels of glyburide and the latter may also diminish gluconeogenic capacity, both of which increase the risk of serious hypoglycemic reactions. Elderly, debilitated or malnourished patients, and those with adrenal or pituitary insufficiency, are particularly susceptible to the hypoglycemic action of glucose-lowering drugs. Hypoglycemia may be difficult to recognize in the elderly and in people who are taking beta-adrenergic blocking drugs. Hypoglycemia is more likely to occur when caloric intake is deficient, after severe or prolonged exercise, when alcohol is ingested, or when more than one glucose lowering drug is used. The risk of hypoglycemia may be increased with combination therapy.

Loss of Control of Blood Glucose

When a patient stabilized on any diabetic regimen is exposed to stress such as fever, trauma, infection or surgery, a loss of control may occur. At such times it may be necessary to discontinue glyburide and administer insulin.

The effectiveness of any hypoglycemic drug, including glyburide, in lowering blood glucose to a desired level decreases in many patients over a period of time which may be due to progression of the severity of diabetes or to diminished responsiveness to the drug. This phenomenon is known as secondary failure, to distinguish it from primary failure in which the drug is ineffective in an individual patient when glyburide is first given. Adequate adjustment of dose and adherence to diet should be assessed before classifying a patient as a secondary failure.

Hemolytic Anemia

Treatment of patients with glucose 6-phosphate dehydrogenase (G6PD) deficiency with sulfonylurea agents can lead to hemolytic anemia. Because glyburide belongs to the class of sulfonylurea agents, caution should be used in patients with G6PD deficiency and a non-sulfonylurea alternative should be considered. In postmarketing reports, hemolytic anemia has also been reported in patients who did not have known G6PD deficiency.

Information for Patients

Patients should be informed of the potential risks and advantages of glyburide and of alternative modes of therapy. They also should be informed about the importance of adherence to dietary instructions, of a regular exercise program, and of regular testing of urine and/or blood glucose.

The risks of hypoglycemia, its symptoms and treatment, and conditions that predispose to its development should be explained to patients and responsible family members. Primary and secondary failure also should be explained.

Physician Counseling Information for Patients

In initiating treatment for type 2 diabetes, diet should be emphasized as the primary form of treatment. Caloric restriction and weight loss are essential in the obese diabetic patient. Proper dietary management alone may be effective in controlling the blood glucose and symptoms of hyperglycemia. The importance of regular physical activity should also be stressed, and cardiovascular risk factors should be identified and corrective measures taken where possible. Use of glyburide or other antidiabetic medications must be viewed by both the physician and patient as a treatment in addition to diet and not as a substitution or as a convenient mechanism for avoiding dietary restraint. Furthermore, loss of blood glucose control on diet alone may be transient, thus requiring only short-term administration of glyburide or other antidiabetic medications. Maintenance or discontinuation of glyburide or other antidiabetic medications should be based on clinical judgment using regular clinical and laboratory evaluations.

Laboratory Tests

Therapeutic response to glyburide tablets should be monitored by frequent urine glucose tests and periodic blood glucose tests. Measurement of glycosylated hemoglobin levels may be helpful in some patients.

Drug Interactions

The hypoglycemic action of sulfonylureas may be potentiated by certain drugs including non-steroidal anti-inflammatory agents and other drugs that are highly protein bound, salicylates, sulfonamides, chloramphenicol, probenecid, coumarins, monoamine oxidase inhibitors, and beta adrenergic blocking agents. When such drugs are administered to a patient receiving glyburide, the patient should be observed closely for hypoglycemia. When such drugs are withdrawn from a patient receiving glyburide, the patient should be observed closely for loss of control.

An increased risk of liver enzyme elevations was observed in patients receiving glyburide concomitantly with bosentan. Therefore concomitant administration of glyburide tablets and bosentan is contraindicated.

Certain drugs tend to produce hyperglycemia and may lead to loss of control. These drugs include the thiazides and other diuretics, corticosteroids, phenothiazines, thyroid products, estrogens, oral contraceptives, phenytoin, nicotinic acid, sympathomimetics, calcium channel blocking drugs, and isoniazid. When such drugs are administered to a patient receiving glyburide, the patient should be closely observed for loss of control. When such drugs are withdrawn from a patient receiving glyburide, the patient should be observed closely for hypoglycemia.

A possible interaction between glyburide and ciprofloxacin, a fluoroquinolone antibiotic, has been reported, resulting in a potentiation of the hypoglycemic action of glyburide. The mechanism for this interaction is not known.

A potential interaction between oral miconazole and oral hypoglycemic agents leading to severe hypoglycemia has been reported. Whether this interaction also occurs with the intravenous, topical or vaginal preparations of miconazole is not known.

Metformin

In a single-dose interaction study in NIDDM subjects, decreases in glyburide AUC and Cmax were observed, but were highly variable. The single-dose nature of this study and the lack of correlation between glyburide blood levels and pharmacodynamic effects, makes the clinical significance of this interaction uncertain. Coadministration of glyburide and metformin did not result in any changes in either metformin pharmacokinetics or pharmacodynamics.

Colesevelam

Concomitant administration of colesevelam and glyburide resulted in reductions in glyburide AUC and Cmax of 32% and 47%, respectively. The reductions in glyburide AUC and Cmax were 20% and 15%, respectively when administered 1 hour before, and not significantly changed (-7% and 4%, respectively) when administered 4 hours before colesevelam.

Topiramate

A drug-drug interaction study conducted in patients with type 2 diabetes evaluated the steady-state pharmacokinetics of glyburide (5 mg/day) alone and concomitantly with topiramate (150 mg/day). There was a 22% decrease in Cmax and a 25% reduction in AUC24 for glyburide during topiramate administration. Systemic exposure (AUC) of the active metabolites, 4-trans-hydroxy-glyburide (M1) and 3-cis-hydroxyglyburide (M2), was also reduced by 13% and 15%, and Cmax was reduced by 18% and 25%, respectively. The steady-state pharmacokinetics of topiramate were unaffected by concomitant administration of glyburide.

Carcinogenesis, Mutagenesis, and Impairment of Fertility

Studies in rats at doses up to 300 mg/kg/day for 18 months showed no carcinogenic effects. Glyburide is nonmutagenic when studied in the Salmonella microsome test (Ames test) and in the DNA damage/alkaline elution assay. No drug related effects were noted in any of the criteria evaluated in the two year oncogenicity study of glyburide in mice.

Pregnancy

Teratogenic Effects

Pregnancy Category B

Reproduction studies have been performed in rats and rabbits at doses up to 500 times the human dose and have revealed no evidence of impaired fertility or harm to the fetus due to glyburide. There are, however, no adequate and well controlled studies in pregnant women. Because animal reproduction studies are not always predictive of human response, this drug should be used during pregnancy only if clearly needed.

Because recent information suggests that abnormal blood glucose levels during pregnancy are associated with a higher incidence of congenital abnormalities, many experts recommend that insulin be used during pregnancy to maintain blood glucose as close to normal as possible.

Nonteratogenic Effects

Prolonged severe hypoglycemia (4 to 10 days) has been reported in neonates born to mothers who were receiving a sulfonylurea drug at the time of delivery. This has been reported more frequently with the use of agents with prolonged half-lives. If glyburide is used during pregnancy, it should be discontinued at least two weeks before the expected delivery date.

Nursing Mothers

Although it is not known whether glyburide is excreted in human milk, some sulfonylurea drugs are known to be excreted in human milk. Because the potential for hypoglycemia in nursing infants may exist, a decision should be made whether to discontinue nursing or to discontinue the drug, taking into account the importance of the drug to the mother. If the drug is discontinued, and if diet alone is inadequate for controlling blood glucose, insulin therapy should be considered.

Pediatric Use

Safety and effectiveness in pediatric patients have not been established.

Geriatric Use

Elderly patients are particularly susceptible to the hypoglycemic action of glucose lowering drugs. Hypoglycemia may be difficult to recognize in the elderly (see PRECAUTIONS). The initial and maintenance dosing should be conservative to avoid hypoglycemic reactions (see DOSAGE AND ADMINISTRATION).

Elderly patients are prone to develop renal insufficiency, which may put them at risk of hypoglycemia. Dose selection should include assessment of renal function.

ADVERSE REACTIONS

Hypoglycemia: See PRECAUTIONS and OVERDOSAGE Sections.

Gastrointestinal Reactions: Cholestatic jaundice and hepatitis may occur rarely which may progress to liver failure; glyburide tablets should be discontinued if this occurs.

Liver function abnormalities, including isolated transaminase elevations, have been reported.

Gastrointestinal disturbances, e.g., nausea, epigastric fullness, and heartburn are the most common reactions, having occurred in 1.8% of treated patients during clinical trials. They tend to be dose related and may disappear when dosage is reduced.

Dermatologic Reactions: Allergic skin reactions, e.g., pruritus, erythema, urticaria, and morbilliform or maculopapular eruptions occurred in 1.5% of treated patients during clinical trials. These may be transient and may disappear despite continued use of glyburide; if skin reactions persist, the drug should be discontinued.

Porphyria cutanea tarda and photosensitivity reactions have been reported with sulfonylureas.

Hematologic Reactions: Leukopenia, agranulocytosis, thrombocytopenia, hemolytic anemia (see PRECAUTIONS), aplastic anemia, and pancytopenia have been reported with sulfonylureas.

Metabolic Reactions: Hepatic porphyria and disulfiram-like reactions have been reported with sulfonylureas; however, hepatic porphyria has not been reported with glyburide and disulfiram-like reactions have been reported very rarely.

Cases of hyponatremia have been reported with glyburide and all other sulfonylureas, most often in patients who are on other medications or have medical conditions known to cause hyponatremia or increase release of antidiuretic hormone. The syndrome of inappropriate antidiuretic hormone (SIADH) secretion has been reported with certain other sulfonylureas, and it has been suggested that these sulfonylureas may augment the peripheral (antidiuretic) action of ADH and/or increase release of ADH.

Other Reactions: Changes in accommodation and/or blurred vision have been reported with glyburide and other sulfonylureas. These are thought to be related to fluctuation in glucose levels.

In addition to dermatologic reactions, allergic reactions such as angioedema, arthralgia, myalgia and vasculitis have been reported.

OVERDOSAGE

Overdosage of sulfonylureas, including glyburide tablets, can produce hypoglycemia. Mild hypoglycemic symptoms, without loss of consciousness or neurological findings, should be treated aggressively with oral glucose and adjustments in drug dosage and/or meal patterns. Close monitoring should continue until the physician is assured that the patient is out of danger. Severe hypoglycemic reactions with coma, seizure, or other neurological impairment occur infrequently, but constitute medical emergencies requiring immediate hospitalization. If hypoglycemic coma is diagnosed or suspected, the patient should be given a rapid intravenous injection of concentrated (50%) glucose solution. This should be followed by a continuous infusion of a more dilute (10%) glucose solution at a rate which will maintain the blood glucose at a level above 100 mg/dL. Patients should be closely monitored for a minimum of 24 to 48 hours, since hypoglycemia may recur after apparent clinical recovery.

DOSAGE AND ADMINISTRATION

Patients should be retitrated when transferred from glyburide (micronized) tablets or other oral hypoglycemic agents (see PRECAUTIONS).

There is no fixed dosage regimen for the management of diabetes mellitus with glyburide tablets. In addition to the usual monitoring of urinary glucose, the patient’s blood glucose must also be monitored periodically to determine the minimum effective dose for the patient; to detect primary failure, i.e., inadequate lowering of blood glucose at the maximum recommended dose of medication; and to detect secondary failure, i.e., loss of adequate blood glucose lowering response after an initial period of effectiveness. Glycosylated hemoglobin levels may also be of value in monitoring the patient’s response to therapy.

Short-term administration of glyburide tablets may be sufficient during periods of transient loss of control in patients usually controlled well on diet.

Usual Starting Dose

The usual starting dose of glyburide tablets is 2.5 to 5 mg daily, administered with breakfast or the first main meal. Those patients who may be more sensitive to hypoglycemic drugs should be started at 1.25 mg daily. (See PRECAUTIONS section for patients at increased risk.) Failure to follow an appropriate dosage regimen may precipitate hypoglycemia. Patients who do not adhere to their prescribed dietary and drug regimen are more prone to exhibit unsatisfactory response to therapy.

Transfer From Other Hypoglycemic Therapy Patients Receiving Other Oral Antidiabetic Therapy

Transfer of patients from other oral antidiabetic regimens to glyburide tablets should be done conservatively and the initial daily dose should be 2.5 to 5 mg. When transferring patients from oral hypoglycemic agents other than chlorpropamide to glyburide tablets, no transition period and no initial or priming dose are necessary. When transferring patients from chlorpropamide, particular care should be exercised during the first two weeks because the prolonged retention of chlorpropamide in the body and subsequent overlapping drug effects may provoke hypoglycemia.

Patients Receiving Insulin

Some Type II diabetic patients being treated with insulin may respond satisfactorily to glyburide tablets. If the insulin dose is less than 20 units daily, substitution of glyburide tablets 2.5 to 5 mg as a single daily dose may be tried. If the insulin dose is between 20 and 40 units daily, the patient may be placed directly on glyburide tablets 5 mg daily as a single dose. If the insulin dose is more than 40 units daily, a transition period is required for conversion to glyburide tablets. In these patients, insulin dosage is decreased by 50% and glyburide tablets 5 mg daily is started. Please refer to Titration to Maintenance Dose for further explanation.

Patients Receiving Colesevelam

When colesevelam is coadministered with glyburide, maximum plasma concentration and total exposure to glyburide is reduced. Therefore, glyburide tablets should be administered at least 4 hours prior to colesevelam.

Titration to Maintenance Dose

The usual maintenance dose is in the range of 1.25 to 20 mg daily, which may be given as a single dose or in divided doses (see Dosage Interval section). Dosage increases should be made in increments of no more than 2.5 mg at weekly intervals based upon the patient’s blood glucose response.

No exact dosage relationship exists between glyburide tablets and the other oral hypoglycemic agents. Although patients may be transferred from the maximum dose of other sulfonylureas, the maximum starting dose of 5 mg of glyburide tablets should be observed. A maintenance dose of 5 mg of glyburide tablets provides approximately the same degree of blood glucose control as 250 to 375 mg chlorpropamide, 250 to 375 mg tolazamide, 500 to 750 mg acetohexamide, or 1000 to 1500 mg tolbutamide.

When transferring patients receiving more than 40 units of insulin daily, they may be started on a daily dose of glyburide tablets 5 mg concomitantly with a 50% reduction in insulin dose. Progressive withdrawal of insulin and increase of glyburide tablets in increments of 1.25 to 2.5 mg every 2 to 10 days is then carried out. During this conversion period when both insulin and glyburide tablets are being used, hypoglycemia may occur. During insulin withdrawal, patients should test their urine for glucose and acetone at least three times daily and report results to their physician. The appearance of persistent acetonuria with glycosuria indicates that the patient is a Type I diabetic who requires insulin therapy.

Concomitant Glyburide and Metformin Therapy

Glyburide tablets should be added gradually to the dosing regimen of patients who have not responded to the maximum dose of metformin monotherapy after four weeks (see Usual Starting Dose and Titration to Maintenance Dose). Refer to metformin package insert.

With concomitant glyburide and metformin therapy, the desired control of blood glucose may be obtained by adjusting the dose of each drug. However, attempts should be made to identify the optimal dose of each drug needed to achieve this goal. With concomitant glyburide and metformin therapy, the risk of hypoglycemia associated with sulfonylurea therapy continues and may be increased. Appropriate precautions should be taken (see PRECAUTIONS section).

Maximum Dose

Daily doses of more than 20 mg are not recommended.

Dosage Interval

Once-a-day therapy is usually satisfactory. Some patients, particularly those receiving more than 10 mg daily, may have a more satisfactory response with twice-a-day dosage.

Specific Patient Populations

Glyburide is not recommended for use in pregnancy or for use in pediatric patients.

In elderly patients, debilitated or malnourished patients, and patients with impaired renal or hepatic function, the initial and maintenance dosing should be conservative to avoid hypoglycemic reactions (see PRECAUTIONS section).

HOW SUPPLIED

Glyburide tablets USP, 5 mg are light-green colored, round, bi-convex, compressed tablets engraved with N horizontal bisect 344 on one side and 5 on the other side. They are supplied as follows:

NDC 68788-4073-3 bottles of 30 tablets

NDC 68788-4073-6 bottles of 60 tablets

NDC 68788-4073-9 bottles of 90 tablets

NDC 68788-4073-1 bottles of 100 tablets

Store at 20° to 25°C (68° to 77°F) [See USP Controlled Room Temperature].

Dispense in tight, light-resistant container as defined in the USP, with a child-resistant closure (as required). Keep container tightly closed.

KEEP THIS AND ALL MEDICATIONS OUT OF THE REACH OF CHILDREN.

Manufactured In Croatia By:

PLIVA HRVATSKA d.o.o.

Zagreb, Croatia

Manufactured For:

TEVA PHARMACEUTICALS USA, INC.

North Wales, PA 19454

Repackaged By: Preferred Pharmaceuticals Inc.

Rev. W 5/2015

Package/Label Display Panel

NDC 68788-4073

GlyBURIDE
Tablets USP
5 mg

Rx only